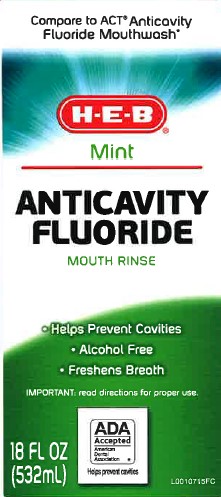 DRUG LABEL: Anticavity Fluoride Rinse
NDC: 37808-213 | Form: MOUTHWASH
Manufacturer: H E B
Category: otc | Type: HUMAN OTC DRUG LABEL
Date: 20260224

ACTIVE INGREDIENTS: SODIUM FLUORIDE 0.2 mg/1 mL
INACTIVE INGREDIENTS: WATER; SORBITOL; MENTHOL, UNSPECIFIED FORM; METHYL SALICYLATE; CETYLPYRIDINIUM CHLORIDE; SACCHARIN SODIUM; POLOXAMER 407; POLYSORBATE 20; PROPYLENE GLYCOL; SODIUM PHOSPHATE; SODIUM PHOSPHATE, DIBASIC, ANHYDROUS; EDETATE CALCIUM DISODIUM ANHYDROUS; EDETATE DISODIUM; SODIUM BENZOATE; POTASSIUM SORBATE; BENZYL ALCOHOL; FD&C GREEN NO. 3; FD&C YELLOW NO. 5

HEB 213.002/213AE Rev 2
Anticavity Fluoride Rinse, Mint

Active ingredient

Sodium Fluoride 0.05% (0.02% w/v fluoride ion)

Purpose

Anticavity Rinse

Use

aids in the prevention of dental cavities

Warning

for this product only

Keep out of reach of children

If more than used for rinsing is accidentally swallowed, seek professional assistance or contact a Poison Control Center immediately.

Directions

- adults and children 6 years of age and older: use once a day after brushing your teeth with a toothpaste.
- remove cap
- pour 10 milliliters (10 mL mark on inside of cap); do not fill above 10 mL mark
- vigorously swish 10 milliliters of rinse between your teeth for 1 minute and then spit out
- do now swallow the rinse
- do not eat or drink for 30 minutes after rinsing
- instruct children under 12 years of age in good rinsing habits (to minimize swallowing)
- supervise children as necessay until capable of using without supervision
- children under 6 years of age: consult a dentist or doctor

other information

- store at room temperature

inactive ingredients

water, sorbitol, menthol, methyl salicylate, flavor, cetylpyridinium chloride, sodium saccharin, poloxamer 407, polysorbate 20, propylene glycol, sodium phosphate, disodium phosphate, calcium disodium EDTA, disodium EDTA, sodium benzoate, potassium sorbate, benzyl alcohol, green 3, yellow 5

Questions?

Call 1-888-593-0593

Disclaimer

*This product is not manufactured or distributed by Chattem, Inc., distributor of Act Anticavity Fluoride Mouthwash

TEP

SEALED WITH PRINTED NECKBAND FOR YOUR PROTECTION

Adverse reactions

MADE WTH PRIDE AND CARE FOR H-E-B SAN ANTONIO, TX 78204

100% Guarantee promise

Principal Display Panel

Compare to ACT Anticavity

Fluoride Mouthwash

H-E-B

Mint

ANTICAVITY

FLUORIDE

MOUTH RINSE

- Helps Prevent Cavities
- Alcohol Free
- Freshens Breath

IMPORTANT: read directions for proper use.

ADA Accepted

American Dental Association

Helps prevent cavities

18 FL OZ (532 mL)